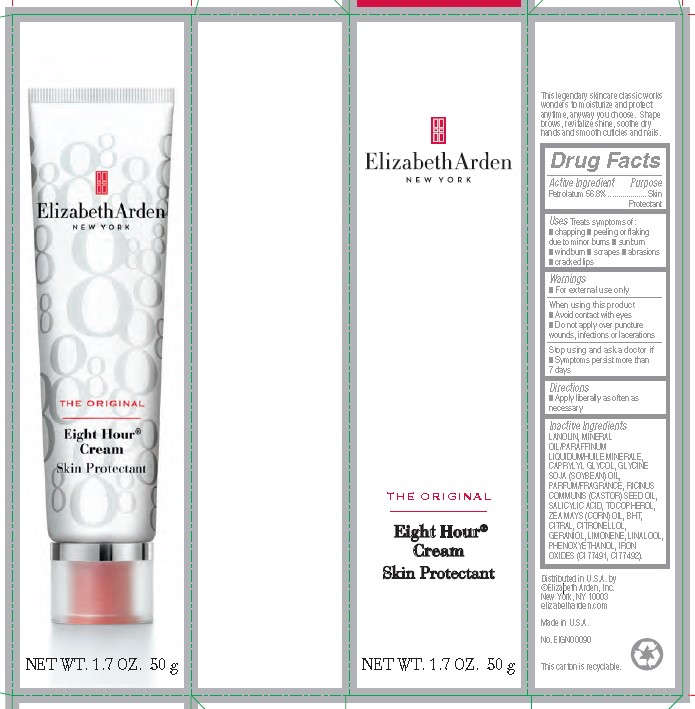 DRUG LABEL: EA EIGHT HOUR SKIN PROTECTANT
NDC: 10967-672 | Form: EMULSION
Manufacturer: REVLON
Category: otc | Type: HUMAN OTC DRUG LABEL
Date: 20250801

ACTIVE INGREDIENTS: PETROLATUM 56.8 mg/1 g
INACTIVE INGREDIENTS: LIMONENE, (+)-; LINALOOL, (+/-)-; LANOLIN; MINERAL OIL; SOYBEAN OIL; FERRIC OXIDE RED; BUTYLATED HYDROXYTOLUENE; GERANIOL; CORN OIL; PHENOXYETHANOL; CASTOR OIL; CITRAL; CAPRYLYL GLYCOL; SALICYLIC ACID; TOCOPHEROL; FERRIC OXIDE YELLOW; .BETA.-CITRONELLOL, (R)-

ELIZABETH ARDEN EIGHT HOUR CREAM SKIN PROTECTANT

ACTIVE INGREDIENTS

Petrolatum 56.8%................... Skin Protectant

OTHER INGREDIENTS

LANOLIN, MINERAL OIL/PARAFFINUM LIQUIDUM/HUILE MINERALE, CAPRYLYL GLYCOL, GLYCINE SOJA (SOYBEAN) OIL, PARFUM/FRAGRANCE, RICINUS COMMUNIS (CASTOR) SEED OIL, SALICYLIC ACID, TOCOPHEROL, ZEA MAYS (CORN) OIL, BHT, CITRAL, CITRONELLOL, GERANIOL, LIMONENE, LINALOOL, PHENOXYETHANOL, IRON OXIDES (CI 77491, CI 77492).

USES

Treats symptoms of:
■ chapping

■ peeling or flaking due to minor burns

■ sunburn
■ windburn

■ scrapes

■ abrasions
■ cracked lips

WARNINGS

■ For external use only

When using this product
■ Avoid contact with eyes
■ Do not apply over puncture wounds, infections or lacerations

Stop using and ask a doctor if
■ Symptoms persist more than 7 days

DIRECTIONS

■ Apply liberally as often as necessary

DOSAGE AND ADMINISTRATION

- Apply liberally as often as necessary

WARNINGS

- For external use only

Uses

Treats symptoms of:

- chapping
- peeling or flaking due to minor burns
- suncrun
- windburn
- scrapes
- abrasions
- cracked lips

KEEP OUT OF REACH OF CHILDREN

NA

PURPOSE

Skin Protectant